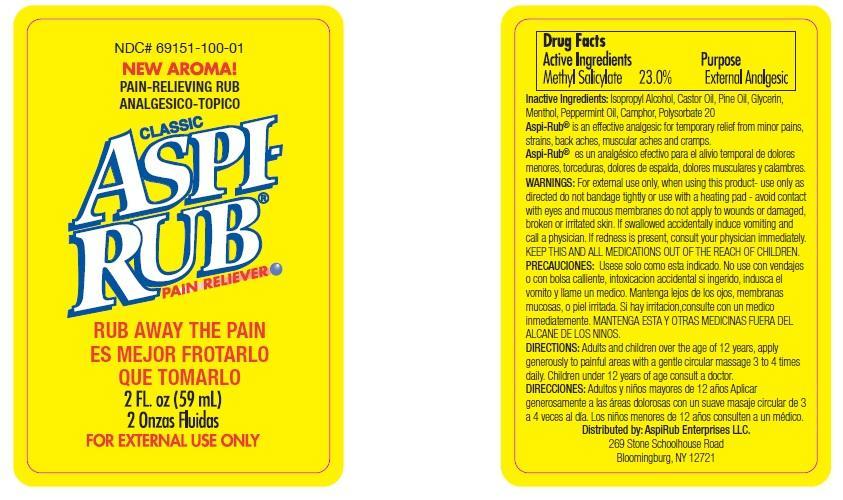 DRUG LABEL: Aspi-Rub
NDC: 69151-100 | Form: SPRAY
Manufacturer: AspiRub Enterprises LLC
Category: otc | Type: HUMAN OTC DRUG LABEL
Date: 20140829

ACTIVE INGREDIENTS: METHYL SALICYLATE 23 g/100 g
INACTIVE INGREDIENTS: ISOPROPYL ALCOHOL; CASTOR OIL; WHITE PINE OIL; GLYCERIN; MENTHOL; PEPPERMINT OIL; CAMPHOR (SYNTHETIC); POLYSORBATE 20

Drug Facts

Active Ingredients

Methyl Salicylate 23.0%

Purpose

External Analgesic

Inactive Ingredients

Isopropyl Alcohol, Castor Oil, Pine Oil, Glycerin, Menthol, Peppermint Oil, Camphor, Polysorbate 20

WARNINGS

For external use only.

When using this product-

use only as directed, do not bandage tightly or use with a heating pad - avoid contact with eye and mucous membranes do not apply to wounds or damaged, broken or irritated skin.

ASK DOCTOR

If swallowed accidentally induce vomiting and call a physician. If redness is present, consult your physician immediately.

KEEP OUT OF REACH OF CHILDREN

KEEP THIS AND ALL MEDICATIONS OUT OF THE REACH OF CHILDREN.

Directions

Adults and children over the age of 12 years, apply generously to painful areas with a gentle circular massage 3 to 4 times daily. Children under 12 years of age consult a doctor.

Principal Display Panel

NDC # 69151-100-01

NEW AROMA!

PAIN-RELIEVING RUB

CLASSIC ASPI-RUB

PAIN RELIEVER

RUB AWAY THE PAIN

2 FL.oz (59 mL)

FOR EXTERNAL USE ONLY

INDICATIONS AND USAGE

Aspi-Rub® is an effective analgesic for temporary relief from minor pains, strains, back aches, muscular aches and cramps.